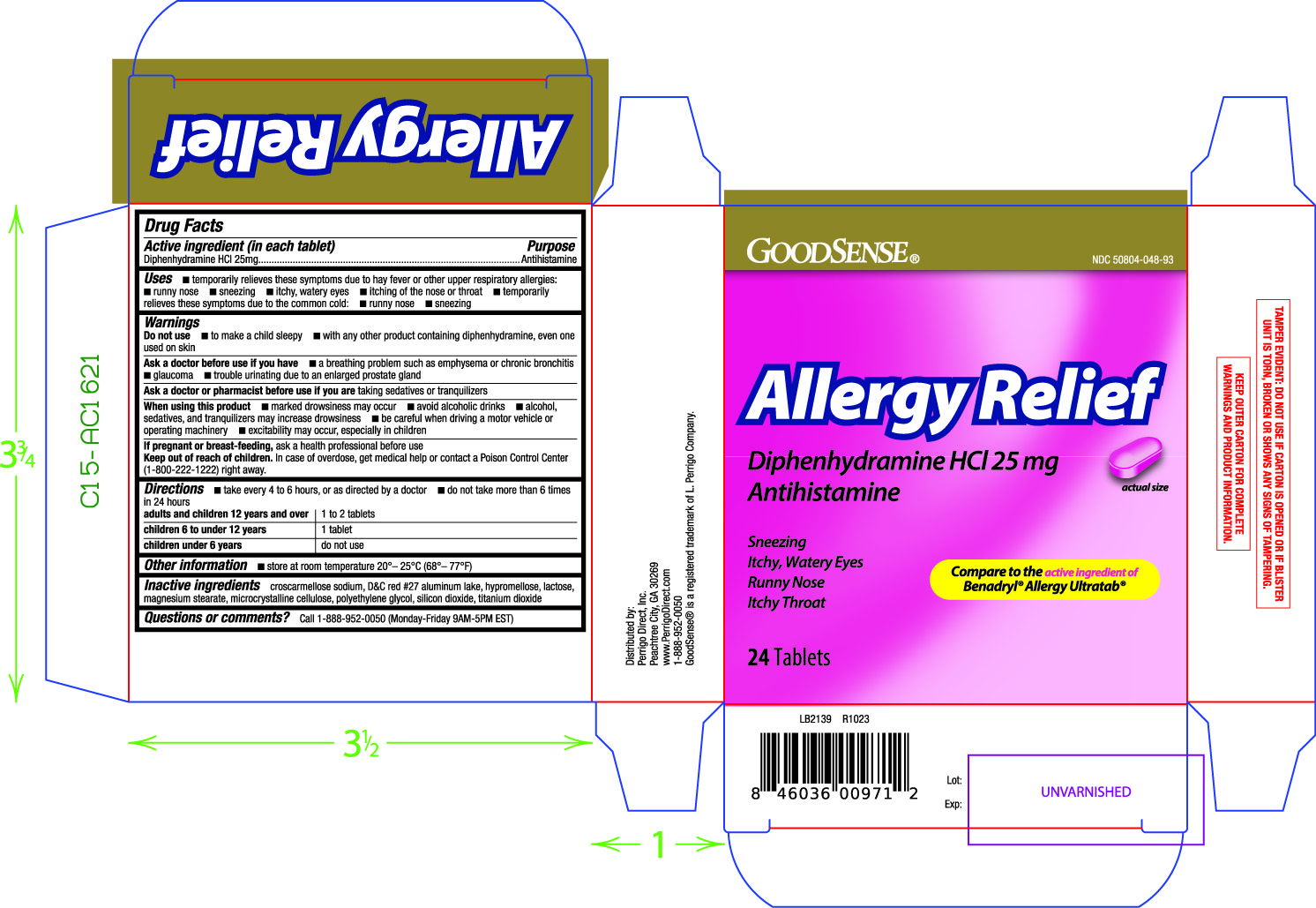 DRUG LABEL: Allergy Relief
NDC: 50804-048 | Form: TABLET
Manufacturer: Good Sense
Category: otc | Type: HUMAN OTC DRUG LABEL
Date: 20240126

ACTIVE INGREDIENTS: DIPHENHYDRAMINE HYDROCHLORIDE 25 mg/1 1
INACTIVE INGREDIENTS: CROSCARMELLOSE SODIUM; D&C RED NO. 27 ALUMINUM LAKE; HYPROMELLOSE, UNSPECIFIED; LACTOSE, UNSPECIFIED FORM; MAGNESIUM STEARATE; MICROCRYSTALLINE CELLULOSE; POLYETHYLENE GLYCOL, UNSPECIFIED; SILICON DIOXIDE; TITANIUM DIOXIDE

048 - Allergy Relief

Active ingredient(s)

Diphenhydramine HCl 25 mg

Purpose

Antihistamine

Use(s)

temporarily relieves these symptoms due to hay fever or other upper respiratory allergies:

- runny nose
- sneezing
- itchy, watery eyes
- itching of the nose or throat

temporarily relieves these symptoms due to the common cold:

- sneezing
- runny nose

Warnings

Do not use

- to make a child sleepy
- with any other product containing diphenhydramine, even one used on skin

Ask a doctor before use if

- a breathing problem such as emphysema or chronic bronchitis
- glaucoma
- trouble urinating due to an enlarged prostate gland

Ask a doctor or pharmacist before use if

are taking sedatives or tranquilizers

When using this product

- marked drowsiness may occur
- avoid alcoholic drinks
- alcohol, sedatives, and tranquilizers may increase drowsiness
- be careful when driving a motor vehicle or operating machinery
- excitability may occur, especially in children

If pregnant or breastfeeding,

ask a health professional before use

Keep out of reach of children

In case of overdose, get medical help or contact a Poison Control Center (1-800-222-1222) right away.

Directions

take every 4 to 6 hours, or as directed by a doctor

do not take more than 6 times in 24 hours

adults and children 12 years and over: 1 to 2 tablets

children 6 to under 12 years: 1 tablet

children under 6 years of age: do not use

Other information

store at room temperature 20°– 25°C (68°– 77°F)

Inactive ingredients

croscarmellose sodium, D&C red #27 aluminum lake, hypromellose, lactose, magnesium
stearate, microcrystalline cellulose, polyethylene glycol, silicon dioxide, titanium dioxide

Questions/Comments

Call 1-888-952-0050 (Monday-Friday 9AM-5PM EST)

Principal Display Panel

Allergy Relief